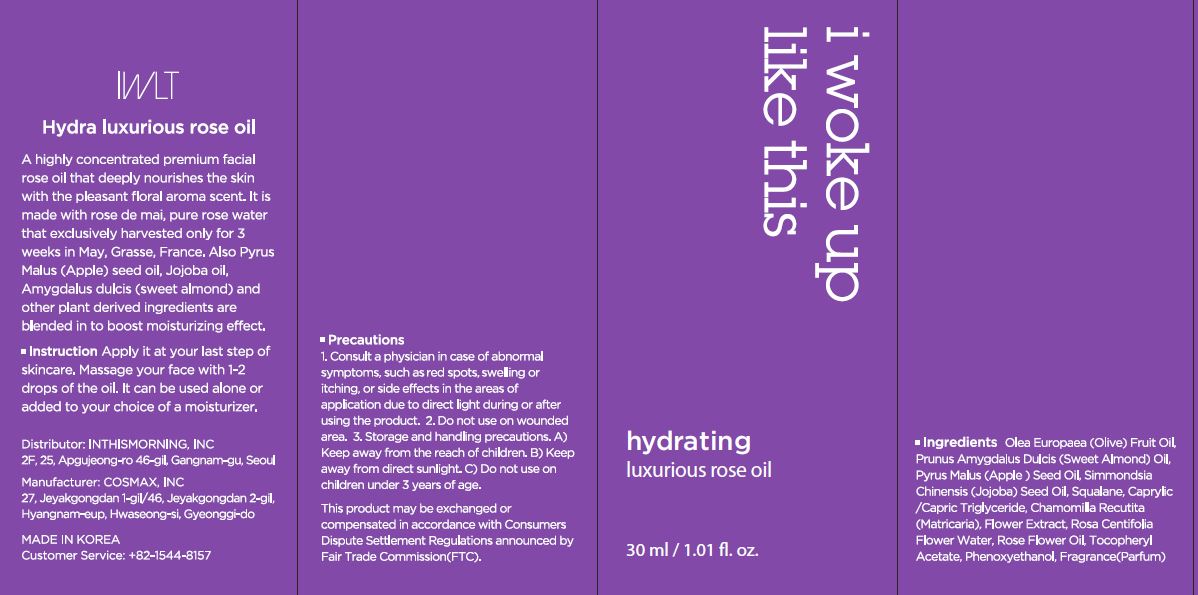 DRUG LABEL: Hydrating luxurious roseoil
NDC: 71217-0049 | Form: OIL
Manufacturer: inthismorning co ltd
Category: otc | Type: HUMAN OTC DRUG LABEL
Date: 20230129

ACTIVE INGREDIENTS: .BETA.-CITRONELLOL, (R)- 0.0090408 g/100 mL; GERANIOL 0.003019675 g/100 mL
INACTIVE INGREDIENTS: OLEA EUROPAEA FRUIT VOLATILE OIL; JOJOBA OIL

Drug Facts

ACTIVE INGREDIENT

citronellol, geraniol

INACTIVE INGREDIENT

Olea Europaea (Olive) Fruit Oil
Prunus Amygdalus Dulcis (Sweet Almond) Oil
Pyrus Malus (Apple) Seed Oil
Simmondsia Chinensis (Jojoba) Seed Oil
Caprylic/Capric Triglyceride
Squalane
Hydrogenated Olive Oil Unsaponifiables
Chamomilla Recutita (Matricaria) Flower Extract
Tocopheryl Acetate
Fragrance(Parfum)
Rosa Centifolia Flower Water
Rose Flower Oil
Phenoxyethanol

PURPOSE

moisturizing

keep out or reach of the children

INDICATIONS AND USAGE

apply it at your last step of skincare,

massage your face with 1-2 drops of the oil

WARNINGS

This product is for exeternal use only. Do not use for internal use
Storage and handling precautions
If possible, avoid direct sunlight and store in cool and area of low humidity in order to maintain the quality of the product and avoid misuse
Avoid placing the product near fire and store out in reach of children

- consult a physician in case of abnormal symptoms, such as red spots, swelling or itching, or side effects in the areas of application due to direct light during or after using the product

- do not use on wounded area

DOSAGE AND ADMINISTRATION

for external use only